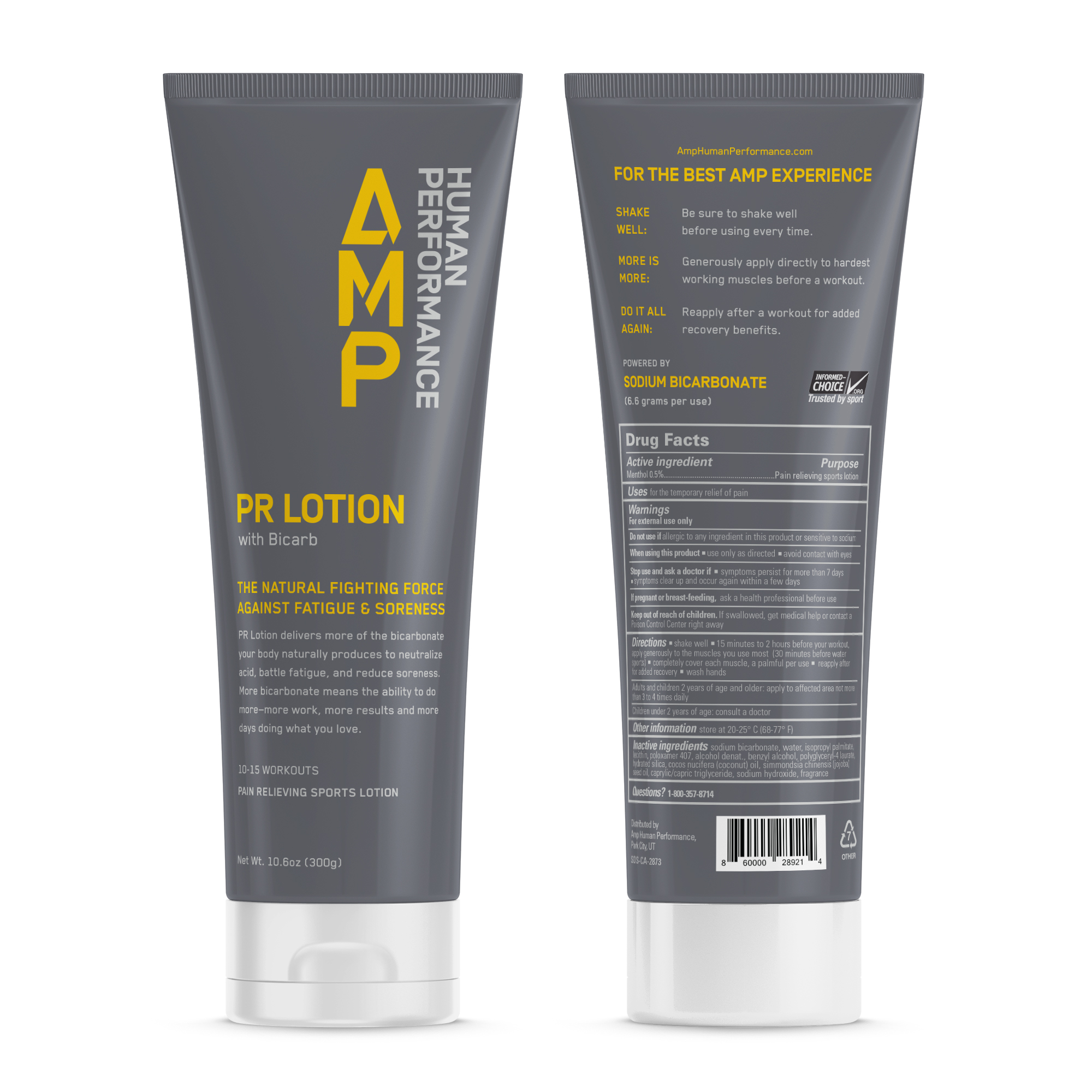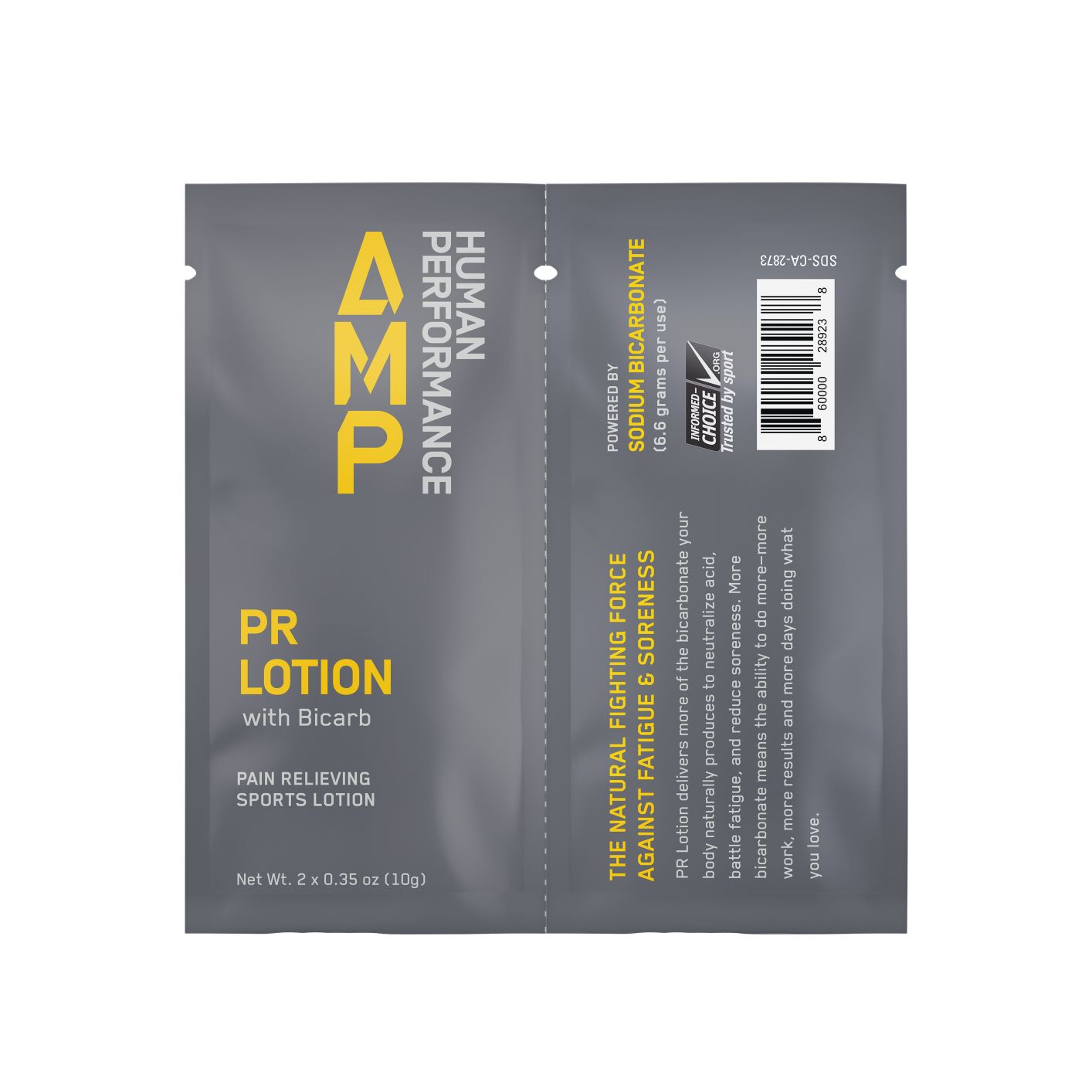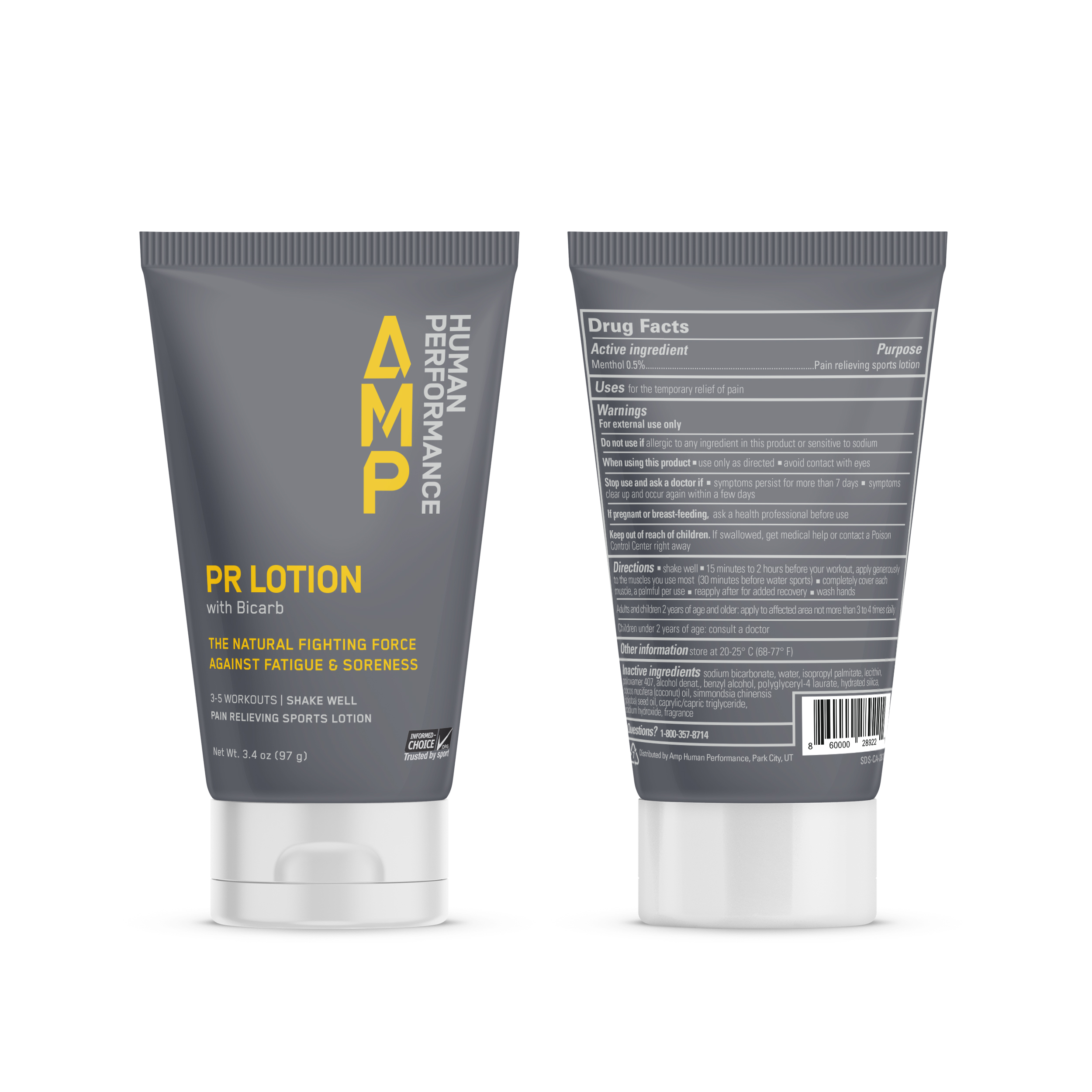 DRUG LABEL: PR
NDC: 72358-101 | Form: LOTION
Manufacturer: Amphp, Inc
Category: otc | Type: HUMAN OTC DRUG LABEL
Date: 20251027

ACTIVE INGREDIENTS: MENTHOL 0.5 g/100 g
INACTIVE INGREDIENTS: JOJOBA OIL; POLYGLYCERYL-3 LAURATE; WATER; ISOPROPYL PALMITATE; COCONUT OIL; SODIUM BICARBONATE; ALCOHOL; BENZYL ALCOHOL; HYDRATED SILICA; LECITHIN, SOYBEAN; POLOXAMER 407; MEDIUM-CHAIN TRIGLYCERIDES; SODIUM HYDROXIDE

ACTIVE INGREDIENT

Menthol 0.5%

PURPOSE

Pain relieving sports lotion

INDICATIONS AND USAGE

For the temporary relief of pain

WARNINGS

For external use only

Do not use if allergic to any ingredient in this product or sensitive to sodium

WHEN USING

Use only as directed. Avoid contact with eyes.

Stop use and ask doctor if:

Symptoms persist for more than 7 days

Symptoms clear up and occur again within a few days

PREGNANCY OR BREAST FEEDING

If pregnant or breast-feeding, ask a health professional before use

Keep out of reach of children. If swallowed, get medical help or contact a poison control center right away.

DOSAGE AND ADMINISTRATION

Shake well. 15 minutes to 2 hours before your workout, apply generously to the muscles you use most (30 minutes before water sports). Completely cover each muscle, a palmful per use. Reapply after for added recovery. Wash hands.

Adults and children 2 years of age or older: apply to affected area not more than 3 to 4 times daily

Children under 2 years of age: consult a doctor

OTHER SAFETY INFORMATION

Store at 20-25C (68-77F)

INACTIVE INGREDIENT

sodium bicarbonate, water, isopropyl palmitate, lecithin, poloxamer 407, alcohol denat., benzyl alcohol, polygylceryl-4 laurate, hydrated silica, cocos nucifera (coconut) oil, simmondsia chinensis (jojoba) seed oil, caprylic/capric triglyceride, sodium hydroxide, fragrance